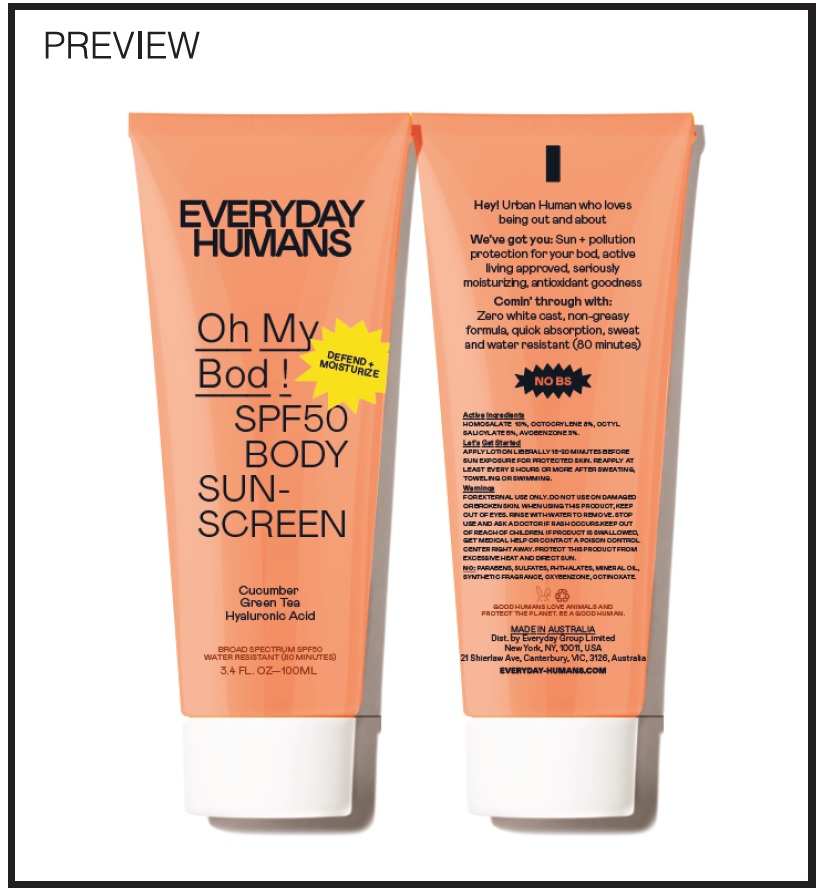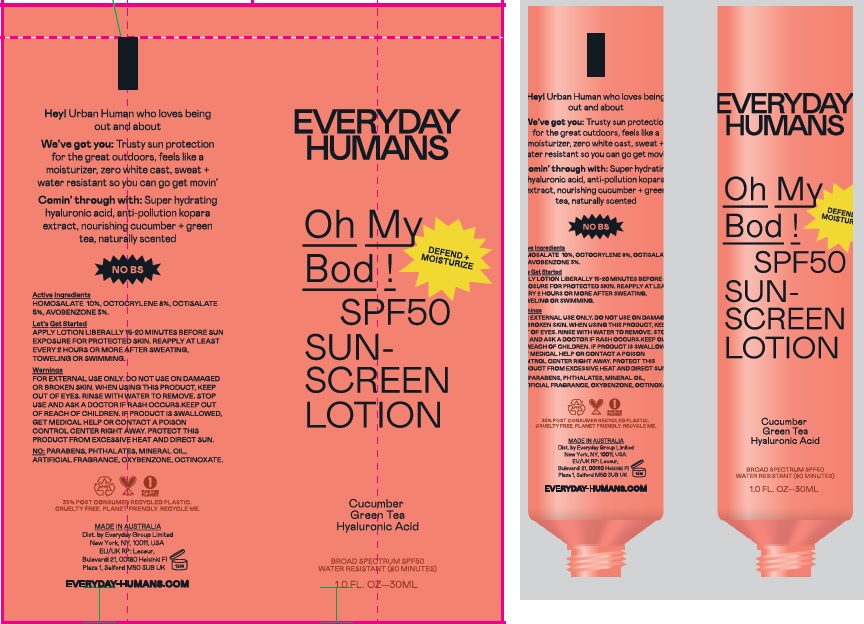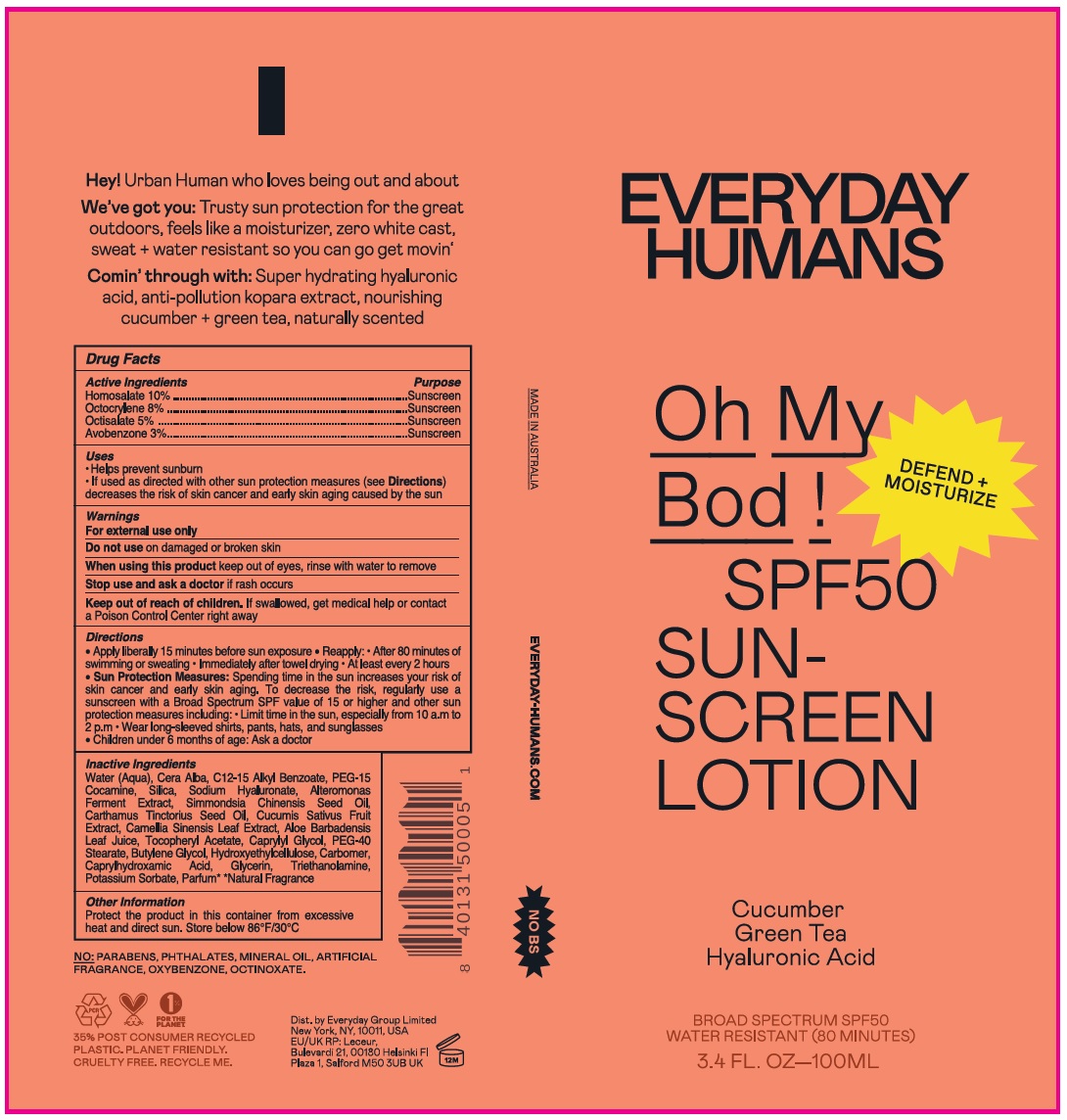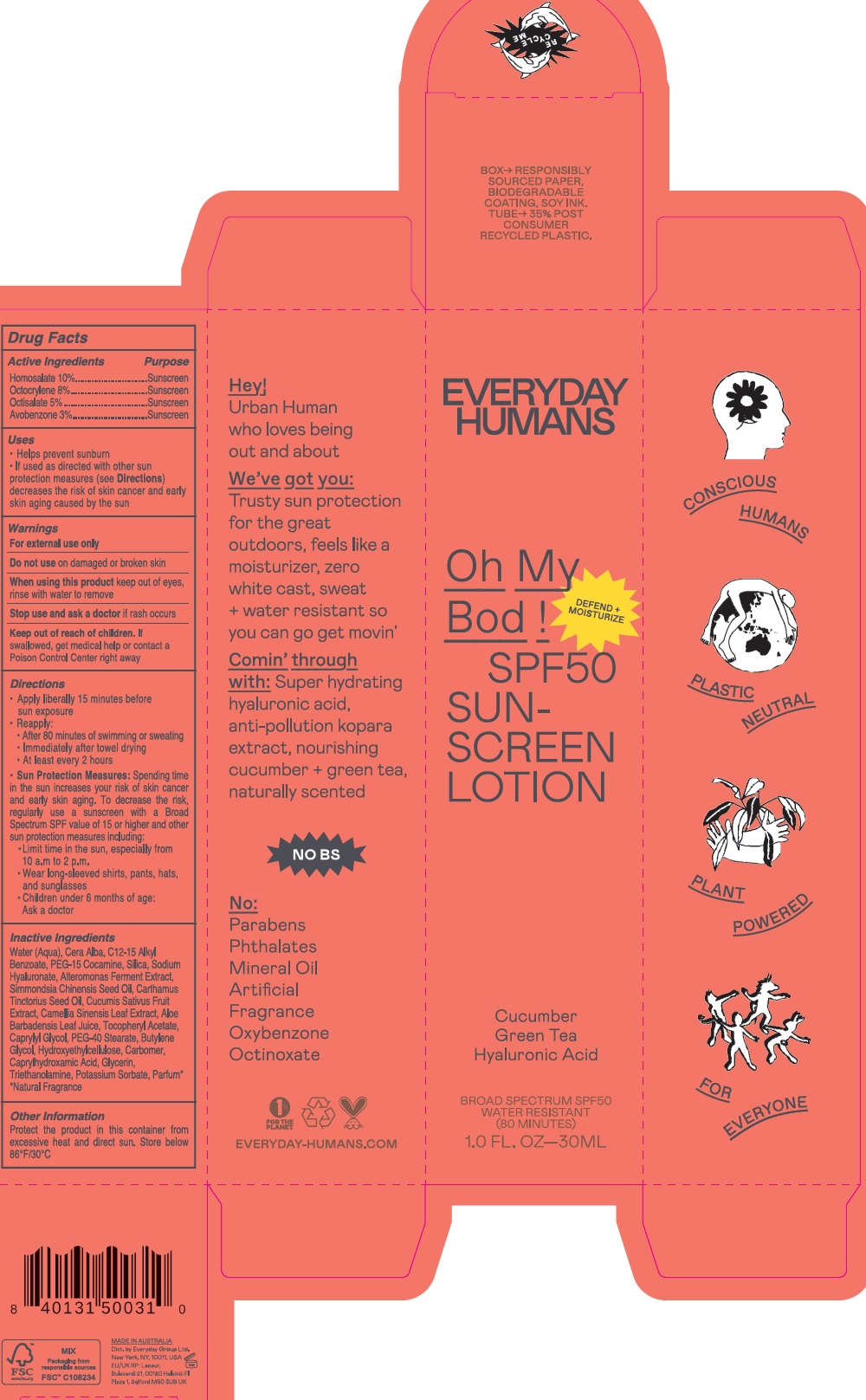 DRUG LABEL: Oh My Bod SPF 50 sunscreen
NDC: 72098-005 | Form: LOTION
Manufacturer: EVERYDAY GROUP LIMITED
Category: otc | Type: HUMAN OTC DRUG LABEL
Date: 20231215

ACTIVE INGREDIENTS: HOMOSALATE 100 mg/1 mL; OCTOCRYLENE 80 mg/1 mL; OCTISALATE 50 mg/1 mL; AVOBENZONE 30 mg/1 mL
INACTIVE INGREDIENTS: WATER; WHITE WAX; ALKYL (C12-15) BENZOATE; PEG-15 COCAMINE; SILICON DIOXIDE; HYALURONATE SODIUM; ALTEROMONAS MACLEODII POLYSACCHARIDES; JOJOBA OIL; SAFFLOWER OIL; GREEN TEA LEAF; ALOE VERA LEAF; .ALPHA.-TOCOPHEROL ACETATE; CAPRYLYL GLYCOL; PEG-40 STEARATE; BUTYLENE GLYCOL; HYDROXYETHYL CELLULOSE, UNSPECIFIED; CARBOMER HOMOPOLYMER, UNSPECIFIED TYPE; CAPRYLHYDROXAMIC ACID; GLYCERIN; TROLAMINE; POTASSIUM SORBATE

Oh My Bod! SPF 50 sunscreen lotion

Active Ingredients

Homosalate 10%

Octocrylene 8%

Octisalate 5%

Avobenzone 3%

Purpose

Sunscreen

Uses

- Helps prevent sunburn
- If used as directed with other sun protection measures (see) decreases the risk of skin cancer and early skin aging caused by the sun Directions

Warnings

For external use only

Do not use

on damaged or broken skin

When using this product

keep out of eyes, rinse with water to remove

Stop use and ask a doctor

if rash occurs

Keep out of reach of children.

If swallowed, get medical help or contact a Poison Control right away

Directions

- Apply liberally 15 minutes before sun exposure
- Reapply:
- After 80 minutes of swimming or sweating
- Immediately after towel drying
- At least every 2 hours
- Spending time in the sun increases your risk of skin cancer and ealy skin aging. To decrease the risk, regularly use a sunscreen with a Broad Spectrum SPF value of 15 or higher and other sun protection measures including: Sun Protection Measures:
- Limit time in the sun, especially from 10 a.m. to 2 p.m.
- Wear long-sleeved shirts, pants, hats, and suglasses
- Children under 6 months of age: Ask a doctor

Inactive Ingredients

Water (Aqua), Cera Alba, C12-15 Alkyl Benzoate, PEG-15 Cocamine, Silica, Sodium Hyaluronate, Alteromonas Ferment Extract, Simmondsia Chinensis Seed Oil, Carthamus Tinctorius Seed Oil, Cucumis Sativus Fruit Extract, Camellia Sinensis Leaf Extract, Aloe Barbadensis Leaf Juice, Tocopheryl Acetate, Caprylyl Glycol, PEG-40 Stearate, Butylene Glycol, Hydroxyethylcellulose, Carbomer, Caprylhydroxamic Acid, Glycerin, Triethanolamine, Potassium Sorbate, Parfum* *Natural Fragrance

Other Information

Protect the product in this container from excessive heat and direct sun. Store below 86°F/30°C